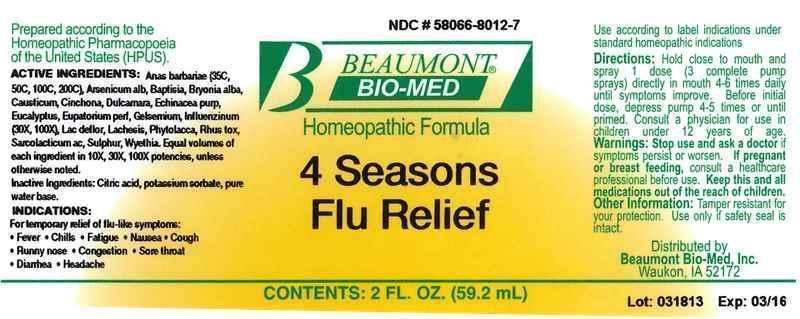 DRUG LABEL: Four Seasons Flu Relief
NDC: 58066-8012 | Form: LIQUID
Manufacturer: Beaumont Bio Med
Category: homeopathic | Type: HUMAN OTC DRUG LABEL
Date: 20150108

ACTIVE INGREDIENTS: CAIRINA MOSCHATA HEART/LIVER AUTOLYSATE 35 [hp_C]/59.2 mL; ARSENIC TRIOXIDE 10 [hp_X]/59.2 mL; BAPTISIA TINCTORIA ROOT 10 [hp_X]/59.2 mL; BRYONIA ALBA ROOT 10 [hp_X]/59.2 mL; CAUSTICUM 10 [hp_X]/59.2 mL; CINCHONA OFFICINALIS BARK 10 [hp_X]/59.2 mL; SOLANUM DULCAMARA TOP 10 [hp_X]/59.2 mL; ECHINACEA PURPUREA 10 [hp_X]/59.2 mL; EUCALYPTUS GLOBULUS LEAF 10 [hp_X]/59.2 mL; EUTROCHIUM PURPUREUM ROOT 10 [hp_X]/59.2 mL; GELSEMIUM SEMPERVIRENS ROOT 10 [hp_X]/59.2 mL; INFLUENZA A VIRUS 10 [hp_X]/59.2 mL; INFLUENZA B VIRUS 10 [hp_X]/59.2 mL; SKIM MILK 10 [hp_X]/59.2 mL; LACHESIS MUTA VENOM 10 [hp_X]/59.2 mL; PHYTOLACCA AMERICANA ROOT 10 [hp_X]/59.2 mL; TOXICODENDRON PUBESCENS LEAF 10 [hp_X]/59.2 mL; LACTIC ACID, L- 10 [hp_X]/59.2 mL; SULFUR 10 [hp_X]/59.2 mL; WYETHIA HELENIOIDES ROOT 10 [hp_X]/59.2 mL
INACTIVE INGREDIENTS: ANHYDROUS CITRIC ACID; POTASSIUM SORBATE; WATER

Four Seasons Flu Relief

ACTIVE INGREDIENT

HPUS active ingredients: Anas barbariae, hepatis et cordis extractum (35C, 50C, 100C, 200C), Arsenicum album, Baptisia tinctoria, Bryonia alba, Causticum, Cinchona officinalis, Dulcamara, Echinacea purpurea, Eucalyptus globulus, Eupatorium purpureum, Gelsemium sempervirens, Influenzinum, Lac defloratum, Lachesis mutus, Phytolacca decandra, Rhus toxicodendron,Sarcolacticum acidum, Sulphur, Wyethia helenioides. Equal volumes of each ingredient in 10X, 30X, 100X potencies, unless otherwise noted.

INACTIVE INGREDIENT

Inactive Ingredients: Citric acid, Potassium sorbate, pure water base.

INDICATIONS AND USAGE

Indications: For temporary relief of flu-like symptoms: • Fever • Fatigue • Nausea • Cough • Runny nose • Congestion • Sore throat • Diarrhea •Headache

Use according to label indications and/or standard homeopathic indications.

DOSAGE AND ADMINISTRATION

Directions: Hold close to mouth and spray 1 dose (3 complete pump sprays) directly in mouth 4-6 times daily until symptoms improve. Before initial dose, depress pump 4-5 times or until primed. Consult a physician for use in children under 12 years of age.

WARNINGS

Warnings: Stop use and ask a doctor if symptoms persist or worsen. If you are pregnant or breast feeding, consult a healthcare professional before use.

- Keep out of reach of children.

OTHER SAFETY INFORMATION

Tamper resistant for your protection. Use only if safety seal is intact.

PURPOSE

For temporary relief of: For temporary relief of flu-like symptoms:

- Fever
- Fatigue
- Nausea
- Cough
- Runny nose
- Congestion
- Sore throat
- Diarrhea
- Headache